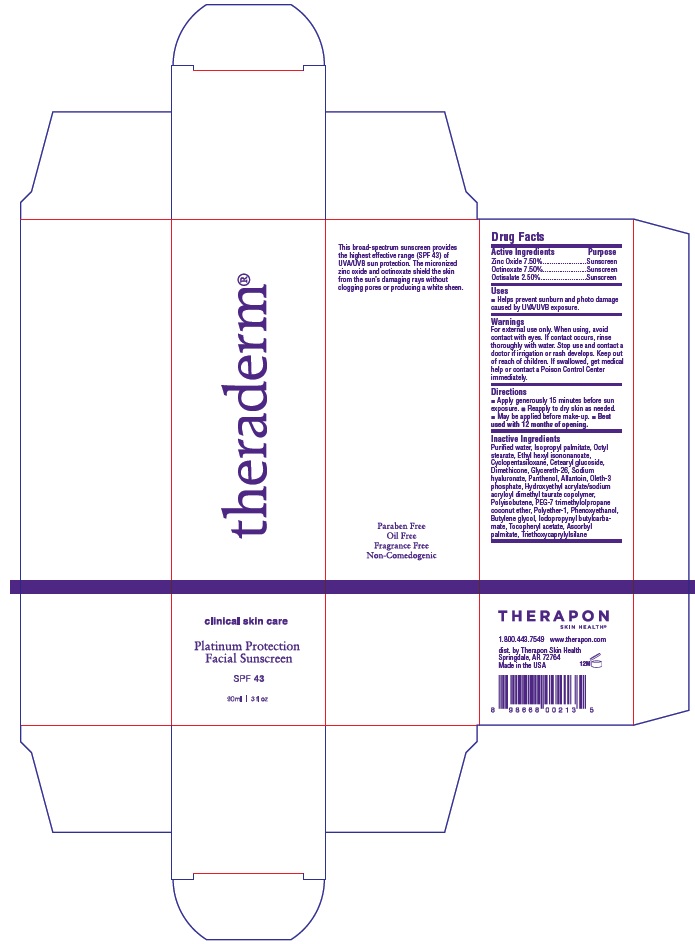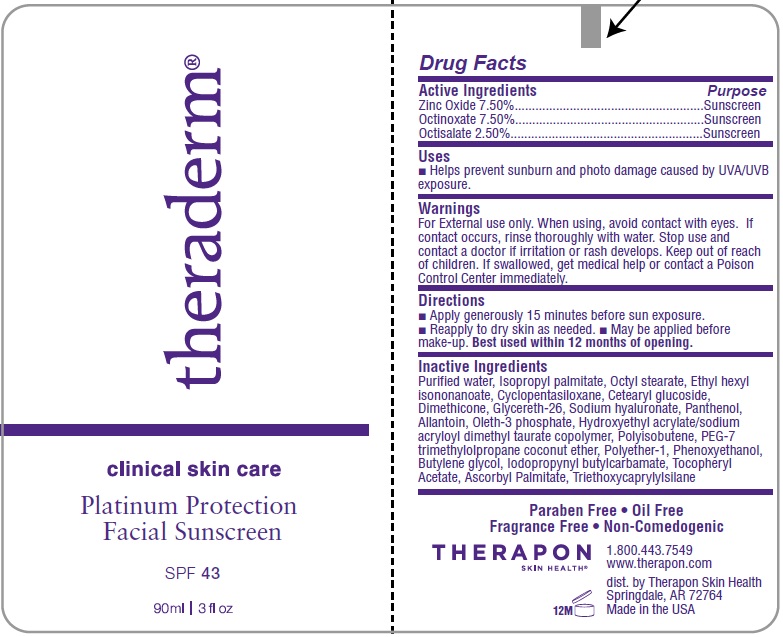 DRUG LABEL: TheradermSPF 43
                  
NDC: 66428-002 | Form: EMULSION
Manufacturer: Therapon Skin Health, LP
Category: otc | Type: HUMAN OTC DRUG LABEL
Date: 20120120

ACTIVE INGREDIENTS: Zinc Oxide 7.5 mL/100 mL; Octinoxate 7.5 mL/100 mL; Octisalate 2.5 mL/100 mL
INACTIVE INGREDIENTS: Water; Isopropyl Palmitate; Octyl Stearate; Ethylhexyl Isononanoate; Cyclomethicone 5  ; Cetearyl Glucoside; Dimethicone; Glycereth-26; Hyaluronate Sodium; Panthenol; Allantoin; Oleth-3 Phosphate; 2-Hydroxyethyl Acrylate; Polyisobutylene (1300 MW); Coconut Alcohol; Polyester-7; Ethylene Oxide; Polyethylene Glycol 350; Polyisobutylene (1300 MW); Phenoxyethanol; Butylene Glycol; Iodopropynyl Butylcarbamate; .Alpha.-Tocopherol Acetate; Ascorbyl Palmitate; Triethoxycaprylylsilane

Theraderm

Active Ingredients

Zinc Oxide 7.50% ...................Sunscreen
Octinoxate 7.50% ...................Sunscreen
Octisalate 2.50% ...................Sunscreen

Uses

Helps prevent sunburn and photo damage caused by UVA/UVB exposure.

Warnings

- For External use only.
- When using, avoid contact with eyes. If contact occurs, rinse thoroughly with water.
- Stop use and contact a doctor if irritation or rash develops.
- Keep out of reach of children. If swallowed, get medical help or contact a Poison Control Center immediately.

Directions

- Apply generously 15 minutes before sun exposure.
- Reapply to dry skin as needed.
- May be applied before make-up

Best used within 12 months of opening.

Inactive Ingredients

Purified water, Isopropyl palmitate, Octyl stearate, Ethyl hexyl isononanoate,Cyclopentasiloxane, Cetearyl glucoside, Dimethicone, Glycereth-26, Sodium Hyaluronate, Panthenol, Allantoin, Oleth-3 phosphate, Hydroxyethyl Acrylate/Sodium acryloyl dimethyl taurate copolymer, Polyisobutene, PEG-7 trimethylolpropane coconut ether, Polyether-1, Phenoxyethanol, Butylene glycol, Iodopropynyl butylcarbamate, Tocopheryl acetate, Triethoxycaprylylsilane.

Label for Tube and Box

Theraderm Tube Label

Theraderm Box Label